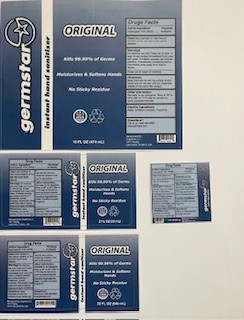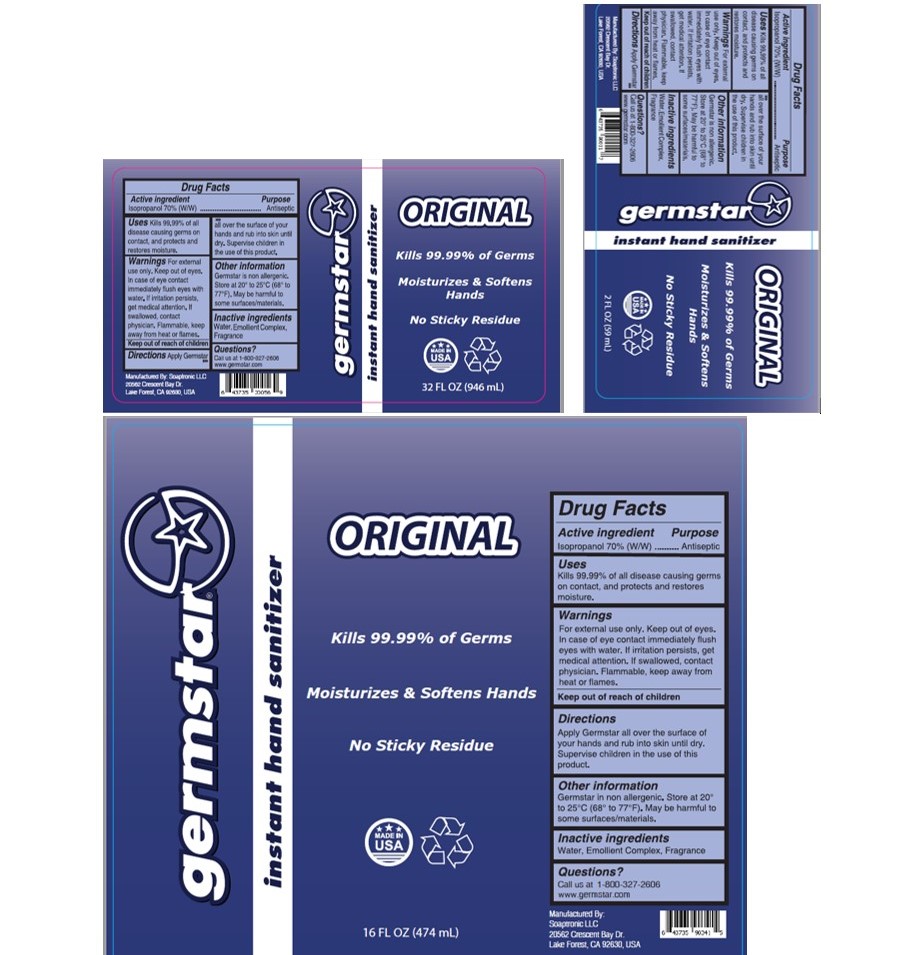 DRUG LABEL: GERMSTARORIGINAL
NDC: 57915-001 | Form: SOLUTION
Manufacturer: Soaptronic, LLC
Category: otc | Type: HUMAN OTC DRUG LABEL
Date: 20250124

ACTIVE INGREDIENTS: ISOPROPYL ALCOHOL 700 g/1000 g
INACTIVE INGREDIENTS: WATER

GERMSTARORIGINAL

Active ingredient

Isopropyl alcohol 70% (W/W)

Purpose

Antiseptic

Uses

Kills 99.99% of all disease causing germs on contact, and protects and restores moisture.

Warnings
For external use only. Keep out of eyes. In case of eye contact immediately flush eyes with water. If irritation persists, get medical attention. If swallowed, contact physician. Flammable, keep away from heat or flames. Germstar Wipes are safe for most surfaces, however can be harmful to some. Test wipe on a non-conspicuous area if unsure.

Keep out of reach of children.

Directions

Apply Germstar all over the surface of your hands and rub into skin until dry. Supervise children in the use of this product.

Other information

Germstar is non allergenic. Store at 20° to 25°C (68° to 77°F). May be harmful to some surfaces/materials.

Inactive ingredients

Water, Emollient Complex, fragrance.

Questions?

Call Germstar at 1-800.327.2606